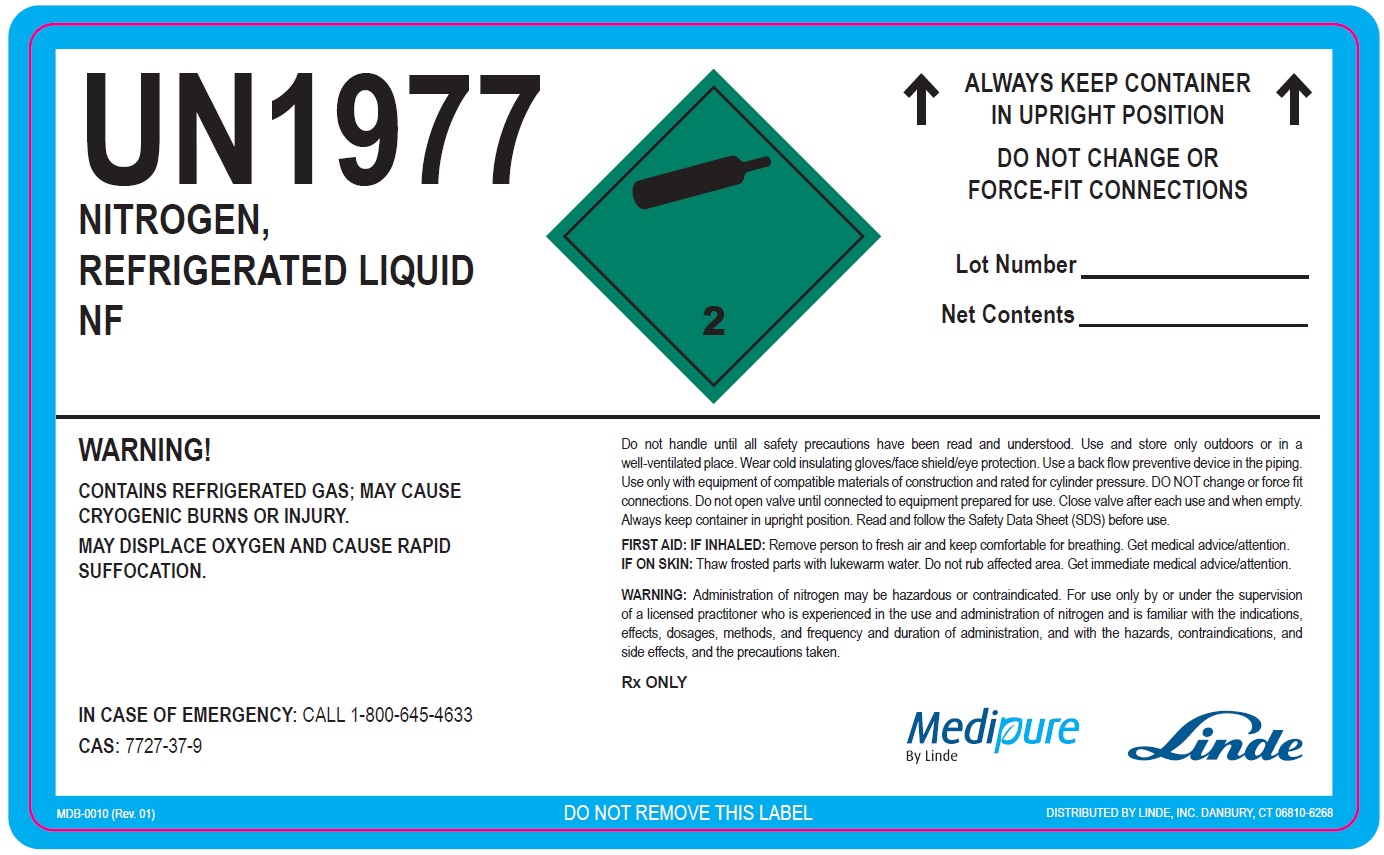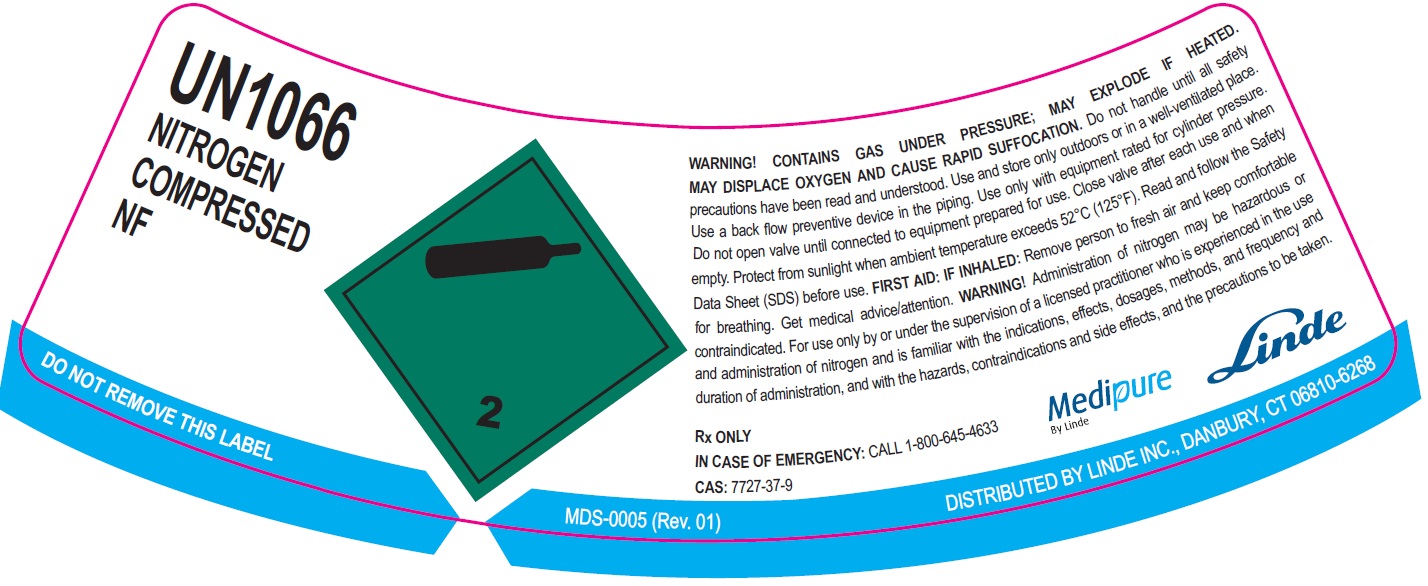 DRUG LABEL: Nitrogen
NDC: 59579-002 | Form: GAS
Manufacturer: Linde Gas & Equipment Inc.
Category: prescription | Type: HUMAN PRESCRIPTION DRUG LABEL
Date: 20250717

ACTIVE INGREDIENTS: NITROGEN 990 mL/1 L

Nitrogen - 002

PACKAGE LABEL

UN1066, COMPRESSED,
NITROGEN,
NF
WARNING! CONTAINS GAS UNDER PRESSURE; MAY EXPLODE IF HEATED
MAY DISPLACE OXYGEN AND CAUSE RAPID SUFFOCATION. Do not handle until all safety
precautions have been read and understood. Use and store only outdoors or in a well-ventilated place.
Use a back flow preventive device in the piping. Use only with equipment rated for cylinder pressure.
Do not open valve until connected to equipment prepared for use. Close valve after each use and when empty.
Protect from sunlight when ambient temperature exceeds 52°C (125°F). Read and follow the Safety
Data Sheet (SDS) before use. FIRST AID: IF INHALED: Remove person to fresh air and keep comfortable for breathing.
Get medical advice/attention. WARNING! Administration of nitrogen may be hazardous or contraindicated.
For use only by or under the supervision of a licensed practitioner who is experienced in the use and
administration of nitrogen and is familiar with the indications, effects, dosages, methods, and frequency and
duration of administration, and with the hazards, contraindications and side effects, and the precautions to be taken.
Rx ONLY
IN CASE OF EMERGENCY: CALL 1-800-645-4633

CAS: 7727-37-9

Medipure by Linde

Linde

DO NOT REMOVE THIS LABEL MDS-0005 (Rev. 01)

DISTRIBUTED BY LINDE, INC., DANBURY CT 06810-6268

PACKAGE LABEL

UN1977, NITROGEN, NF

REFRIGERATED LIQUID

NF
↑ALWAYS KEEP CONTINER IN UPRIGHT POSITION↑

DO NOT CHANGE OR FORCE-FIT CONNECTIONS
LOT Number ________
NET CONTENTS ________
WARNING! CONTAINS REFIGERATED GAS; MAY CAUSE CRYOGENIC BURNS OR INJURY. MAY DISPLACE OXYGEN AND CAUSE RAPID SUFFOCATION.

Do not handle until safety precautions have read and understood. Use and store only outdoors or in a well-vetilated place. Wear cold insulating gloves/face shield/ eye protection. Use a back flow preventive device in the piping. DO NOT change or force fit connections. Close valve after each use and when empty. Always keep container in upright position. Read and follow the Safety Data Sheet (SDS) before use.

FIRST AID: IF INHALED:Remove person to fresh air and keep comfortable for breathing. IF ON SKIN:Thaw frosted parts with lukewarm water. Do not rub affected area. Get immediate medical advice/attention.

WARNING:Administration of nitrogen may be hazardous or contraindicated. For use only by or under the supervision of a licensed practitioner who is experienced in the use and administration of nitrogen and is familiar with the indications, effects, dosages, methods, and frequency and duration of administration, and with the hazards, contraindications, and side effects and the precautions to be taken.

RX only
IN CASE OF EMERGENCY:CALL 1-800-645-4633
CAS:7727-37-9

Medipure™
By Linde

Linde
MDB-0010 (Rev. 01)

DO NOT REMOVE THIS LABEL
DISTRIBUTED BY Linde, INC.
DANBURY, CT 06810-6268